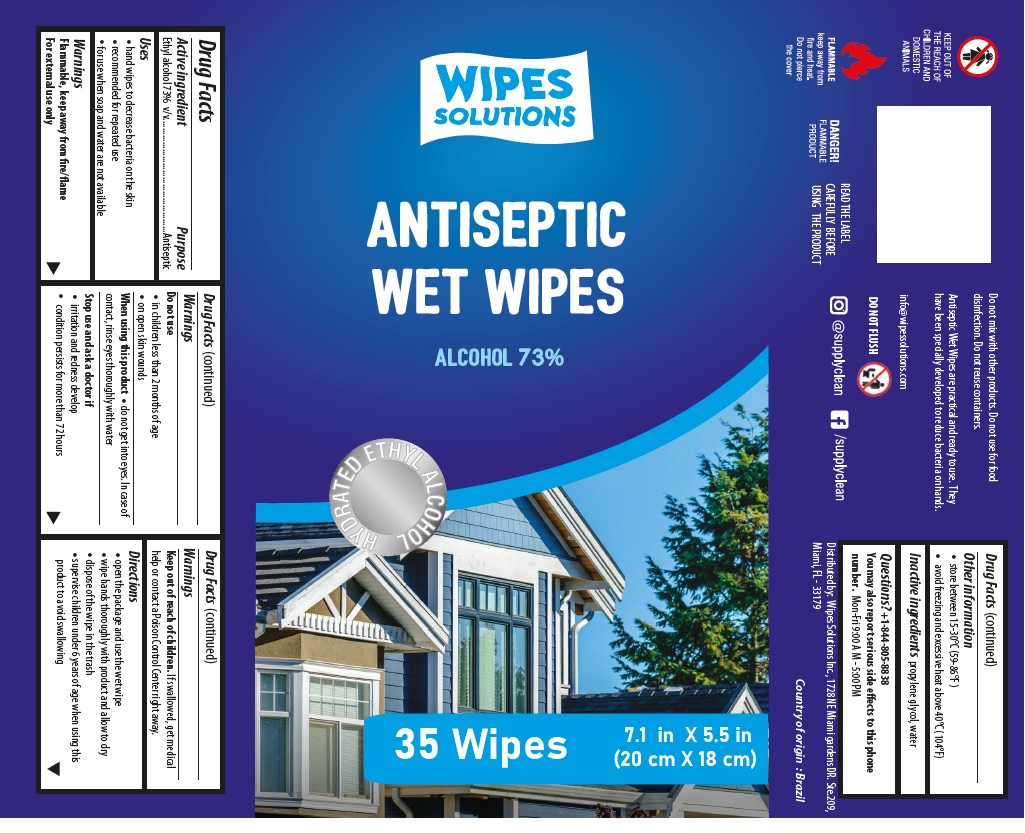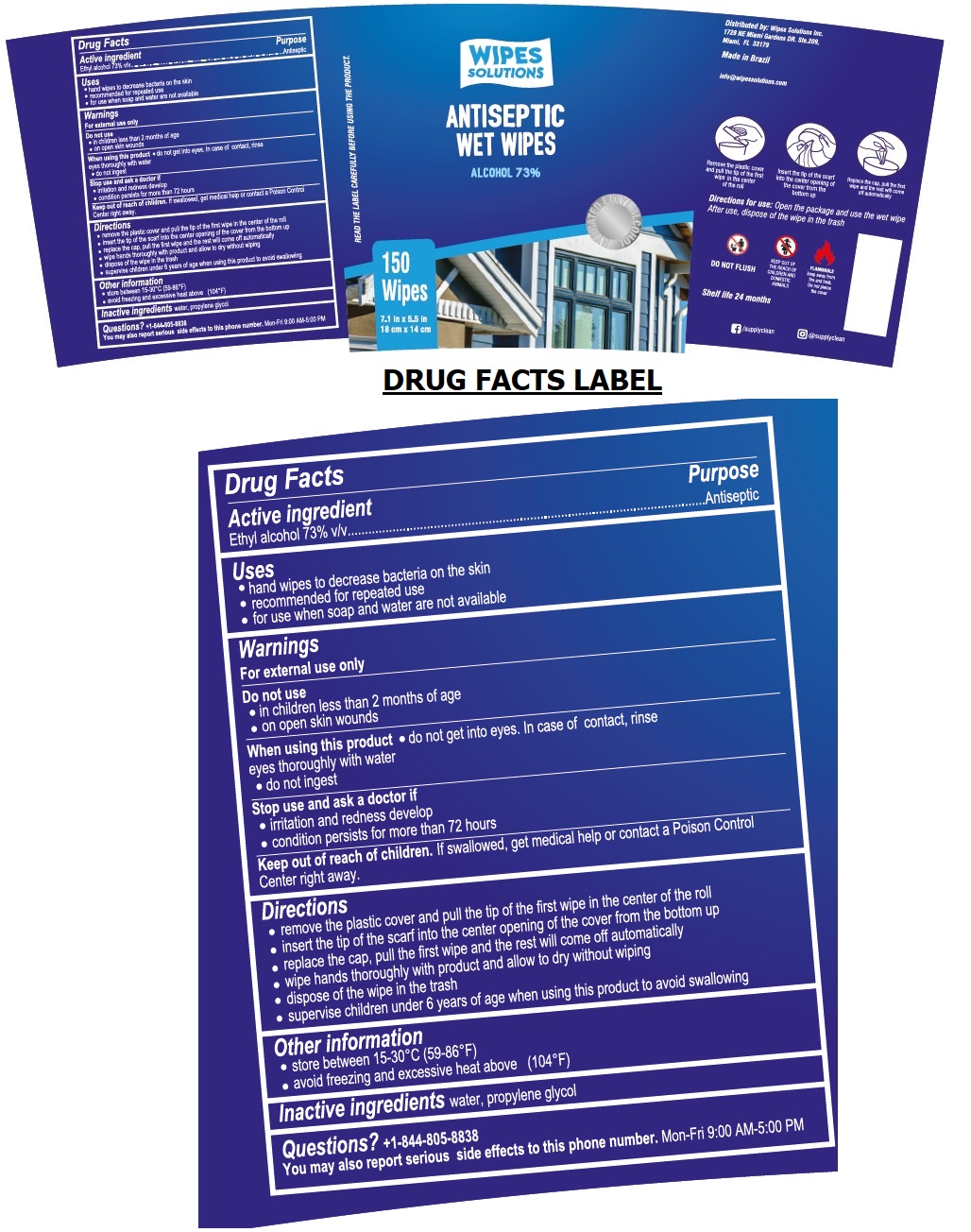 DRUG LABEL: Wipes Solutions Antiseptic Wet Wipes
NDC: 80310-018 | Form: CLOTH
Manufacturer: Supplyclean Industria de Produtos de Higiene S/A
Category: otc | Type: HUMAN OTC DRUG LABEL
Date: 20200828

ACTIVE INGREDIENTS: ALCOHOL 73 mL/100 mL
INACTIVE INGREDIENTS: WATER; PROPYLENE GLYCOL

WIPES SOLUTIONS ANTISEPTIC WET WIPES

Active ingredient

Ethyl alcohol 73% v/v

Purpose

Antiseptic

Uses

• hand wipes to decrease bacteria on the skin

• recommended for repeated use

• for use when soap and water are not available

Warnings

Flammable, keep away from fire/flame

For external use only

Do not use

• in children less than 2 months of age

• on open skin wounds

When using this product • do not get into eyes. In case of contact, rinse eyes thoroughly with water

• do not ingest

Stop use and ask a doctor if

• irritation and redness develop

• condition persists for more than 72 hours

Keep out of reach of children. If swallowed, get medical help or contact a Poison Control Center right away.

Directions

• remove the plastic cover and pull the tip of the first wipe in the center of the roll

• insert the tip of the scarf into the center opening of the cover from the bottom up

• replace the cap, pull the first wipe and the rest will come off automatically

• wipe hands thoroughly with product and allow to dry without wiping

• dispose of the wipe in the trash

• supervise children under 6 years of age when using this product to avoid swallowing

Other information

• store between 15-30°C (59-86°F)

• avoid freezing and excessive heat above (104°F)

Inactive ingredients water, propylene glycol

ALCOHOL 73%

HYDRATED ETHYL ALCOHOL

READ THE LABEL CAREFULLY BEFORE USING THE PRODUCT

Distributed by: Wipes Solutions Inc.

1728 NE Miami Gardens DR. Ste.209,

Miami, FL 33179

Made in Brazil

info@wipessolutions.com

Directions for use: Open the package and use the wet wipe After use, dispose of the wipe in the trash

DO NOT FLUSH

KEEP OUT OF THE REACH OF CHILDREN AND DOMESTIC ANIMALS

FLAMMABLE

keep away from fire and heat. Do not pierce the cover

Shelf life 24 months

/supplyclean

@supplyclean